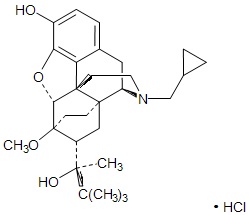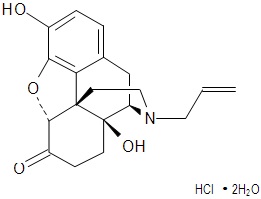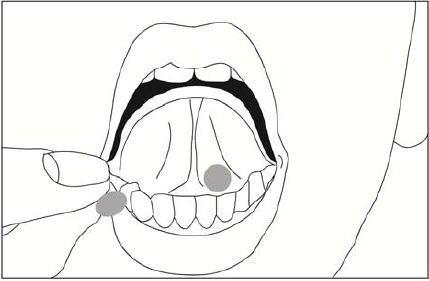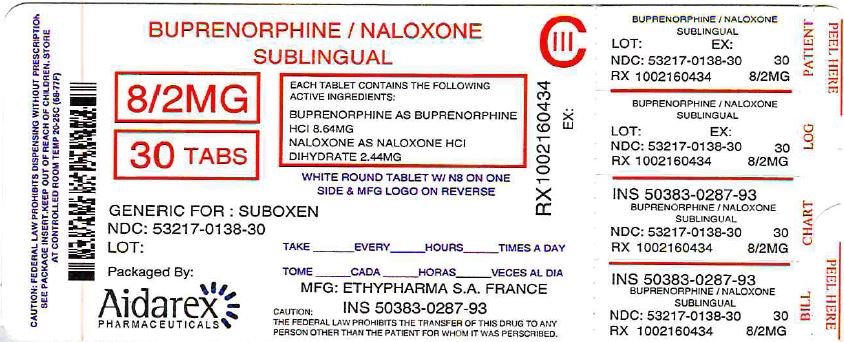 DRUG LABEL: Buprenorphine and Naloxone
NDC: 53217-138 | Form: TABLET
Manufacturer: Aidarex Pharmaceuticals LLC
Category: prescription | Type: HUMAN PRESCRIPTION DRUG LABEL
Date: 20161206
DEA Schedule: CIII

ACTIVE INGREDIENTS: BUPRENORPHINE HYDROCHLORIDE 8 mg/1 1; NALOXONE HYDROCHLORIDE 2 mg/1 1
INACTIVE INGREDIENTS: LACTOSE MONOHYDRATE; MANNITOL; STARCH, CORN; POVIDONE K30; WATER; ANHYDROUS CITRIC ACID; SODIUM CITRATE; SODIUM STEARYL FUMARATE; ACESULFAME POTASSIUM

HIGHLIGHTS OF PRESCRIBING INFORMATION

These highlights do not include all the information needed to use BUPRENORPHINE AND NALOXONE SUBLINGUAL TABLETS safely and effectively. See full prescribing information for BUPRENORPHINE AND NALOXONE SUBLINGUAL TABLETS.
BUPRENORPHINE AND NALOXONE Sublingual Tablets for sublingual administration CIII
Initial U.S. Approval: 2002

RECENT MAJOR CHANGES

Warnings and Precautions Neonatal Opioid Withdrawal Syndrome (5.5) | 11/2016
Adrenal Insufficiency (5.6) | 11/2016

1 INDICATIONS AND USAGE

Buprenorphine and Naloxone Sublingual Tablets are indicated for the maintenance treatment of opioid dependence. Prescription use of this product is limited under the Drug Addiction Treatment Act. (1)

2 DOSAGE AND ADMINISTRATION

Administer Buprenorphine and Naloxone Sublingual Tablets sublingually as a single daily dose. (2)

The recommended daily dose for maintenance is 16 mg/4 mg.

3 DOSAGE FORMS AND STRENGTHS

Sublingual tablet: 2 mg buprenorphine with 0.5 mg naloxone and 8 mg buprenorphine with 2 mg naloxone. (3)

4 CONTRAINDICATIONS

Hypersensitivity to buprenorphine or naloxone. (4)

5 WARNINGS AND PRECAUTIONS

- Buprenorphine can be abused in a similar manner to other opioids. Clinical monitoring appropriate to the patient’s level of stability is essential. Multiple refills should not be prescribed early in treatment or without appropriate patient follow-up visits. (5.1)
- Significant respiratory depression and death have occurred in association with buprenorphine, particularly when taken by the intravenous (IV) route in combination with benzodiazepines or other CNS depressants (including alcohol). (5.2)
- Consider dose reduction of CNS depressants, Buprenorphine and Naloxone Sublingual Tablets, or both in situations of concomitant prescription. (5.3)
- Store Buprenorphine and Naloxone Sublingual Tablets safely out of the sight and reach of children. Buprenorphine can cause severe, possibly fatal, respiratory depression in children. (5.4)
- Neonatal opioid withdrawal syndrome (NOWS) is an expected and treatable outcome of prolonged use of opioids during pregnancy (5.5)
- Adrenal Insufficiency: If diagnosed, treat with physiologic replacement of corticosteroids, and wean patient off the opioid. (5.6)
- Chronic administration produces opioid-type physical dependence. Abrupt discontinuation or rapid dose taper may result in opioid withdrawal syndrome. (5.7)
- Monitor liver function tests prior to initiation and during treatment and evaluate suspected hepatic events. (5.8)
- Do not administer Buprenorphine and Naloxone Sublingual Tablets to patients with known hypersensitivity to buprenorphine or naloxone. (5.9)
- A marked and intense opioid withdrawal syndrome is highly likely to occur with parenteral misuse of Buprenorphine and Naloxone
- Sublingual Tablets by individuals physically dependent on full opioid agonists or by sublingual administration before the agonist effects of other opioids have subsided. (5.10)
- Buprenorphine and Naloxone Sublingual Tablets are not appropriate as an analgesic. There have been reported deaths of opioid naïve individuals who received a 2 mg sublingual dose. (5.11)
- Buprenorphine/naloxone products are not recommended in patients with severe hepatic impairment and may not be appropriate for patients with moderate hepatic impairment. (5.12)
- Caution patients about the risk of driving or operating hazardous machinery. (5.13)

6 ADVERSE REACTIONS

Adverse events commonly observed with the sublingual administration of the Buprenorphine and Naloxone Sublingual Tablets during clinical trials and post-marketing experience are headache, nausea, vomiting, hyperhidrosis, constipation, signs and symptoms of withdrawal, insomnia, pain, and peripheral edema. (6.1 and 6.2)

To report SUSPECTED ADVERSE REACTIONS, contact Hi-Tech Pharmacal Co., Inc. at 1-888-775-1770 or FDA at 1-800-FDA-1088, or www.fda.gov/medwatch.

7 DRUG INTERACTIONS

- Monitor patients starting or ending CYP3A4 inhibitors or inducers for potential over- or underdosing. (7.1)
- Use caution in prescribing Buprenorphine and Naloxone Sublingual Tablets for patients receiving benzodiazepines or other CNS depressants and warn patients against concomitant self-administration/misuse. (7.3)
- Serotonergic Drugs: Concomitant use may result in serotonin syndrome. Discontinue Buprenorphine and Naloxone Sublingual Tablets if serotonin syndrome is suspected. (7.4)

8 USE IN SPECIFIC POPULATIONS

- Pregnancy: Based on animal data, may cause fetal harm. (8.1)
- Nursing mothers: Caution should be exercised when administered to a nursing woman. (8.3)
- Safety and effectiveness of Buprenorphine and Naloxone Sublingual Tablets in patients below the age of 16 has not been established. (8.4)
- Administer Buprenorphine and Naloxone Sublingual Tablets with caution to elderly or debilitated patients. (8.5)
- Buprenorphine/naloxone products are not recommended in patients with severe hepatic impairment and may not be appropriate for patients with moderate hepatic impairment. (8.6)

FULL PRESCRIBING INFORMATION

1 INDICATIONS AND USAGE

Buprenorphine and Naloxone Sublingual Tablets are indicated for the maintenance treatment of opioid dependence and should be used as part of a complete treatment plan to include counseling and psychosocial support.

Under the Drug Addiction Treatment Act (DATA) codified at 21 U.S.C. 823(g), prescription use of this product in the treatment of opioid dependence is limited to physicians who meet certain qualifying requirements, and who have notified the Secretary of Health and Human Services (HHS) of their intent to prescribe this product for the treatment of opioid dependence and have been assigned a unique identification number that must be included on every prescription.

2 DOSAGE AND ADMINISTRATION

Buprenorphine and Naloxone Sublingual Tablets are administered sublingually as a single daily dose. Buprenorphine and Naloxone Sublingual Tablets should be used in patients who have been initially inducted using buprenorphine sublingual tablets.

Medication should be prescribed in consideration of the frequency of visits. Provision of multiple refills is not advised early in treatment or without appropriate patient follow-up visits.

2.1 Maintenance

- Buprenorphine and Naloxone Sublingual Tablets are indicated for maintenance treatment. The recommended target dosage of Buprenorphine and Naloxone Sublingual Tablets are 16 mg/4 mg buprenorphine/naloxone/day as a single daily dose.
- The dosage of Buprenorphine and Naloxone Sublingual Tablets should be progressively adjusted in increments/decrements of 2 mg/0.5 mg or 4 mg/1 mg buprenorphine/naloxone to a level that holds the patient in treatment and suppresses opioid withdrawal signs and symptoms.
- The maintenance dose of Buprenorphine and Naloxone Sublingual Tablets are generally in the range of 4 mg/1 mg buprenorphine/naloxone to 24 mg/6 mg buprenorphine/naloxone per day depending on the individual patient. Dosages higher than this have not been demonstrated to provide any clinical advantage.

2.2 Method of Administration

Buprenorphine and Naloxone Sublingual Tablets should be placed under the tongue until they are dissolved. For doses requiring the use of more than two tablets, patients are advised to either place all the tablets at once or alternatively (if they cannot fit in more than two tablets comfortably), place two tablets at a time under the tongue. Either way, the patients should continue to hold the tablets under the tongue until they dissolve; swallowing the tablets reduces the bioavailability of the drug. To ensure consistency in bioavailability, patients should follow the same manner of dosing with continued use of the product.

Proper administration technique should be demonstrated to the patient.

2.3 Clinical Supervision

Treatment should be initiated with supervised administration, progressing to unsupervised administration as the patient’s clinical stability permits. Buprenorphine and Naloxone Sublingual Tablets are subject to diversion and abuse. When determining the prescription quantity for unsupervised administration, consider the patient’s level of stability, the security of his or her home situation, and other factors likely to affect the ability to manage supplies of take-home medication.

Ideally patients should be seen at reasonable intervals (e.g., at least weekly during the first month of treatment) based upon the individual circumstances of the patient. Medication should be prescribed in consideration of the frequency of visits. Provision of multiple refills is not advised early in treatment or without appropriate patient follow-up visits. Periodic assessment is necessary to determine compliance with the dosing regimen, effectiveness of the treatment plan, and overall patient progress.

Once a stable dosage has been achieved and patient assessment (e.g., urine drug screening) does not indicate illicit drug use, less frequent follow-up visits may be appropriate. A once-monthly visit schedule may be reasonable for patients on a stable dosage of medication who are making progress toward their treatment objectives. Continuation or modification of pharmacotherapy should be based on the physician’s evaluation of treatment outcomes and objectives such as:

1. Absence of medication toxicity
2. Absence of medical or behavioral adverse effects
3. Responsible handling of medications by the patient
4. Patient’s compliance with all elements of the treatment plan (including recovery-oriented activities, psychotherapy, and/or other psychosocial modalities)
5. Abstinence from illicit drug use (including problematic alcohol and/or benzodiazepine use)

If treatment goals are not being achieved, the physician should re-evaluate the appropriateness of continuing the current treatment.

2.4 Unstable Patients

Physicians will need to decide when they cannot appropriately provide further management for particular patients. For example, some patients may be abusing or dependent on various drugs, or unresponsive to psychosocial intervention such that the physician does not feel that he/she has the expertise to manage the patient. In such cases, the physician may want to assess whether to refer the patient to a specialist or more intensive behavioral treatment environment. Decisions should be based on a treatment plan established and agreed upon with the patient at the beginning of treatment.

Patients who continue to misuse, abuse, or divert buprenorphine products or other opioids should be provided with, or referred to, more intensive and structured treatment.

2.5 Patients With Hepatic Impairment

Because the doses of this fixed combination product cannot be individually titrated, severe hepatic impairment results in a reduced clearance of naloxone to a much greater extent than buprenorphine, and moderate hepatic impairment also results in a reduced clearance of naloxone to a greater extent than buprenorphine, the combination product should generally be avoided in patients with severe hepatic impairment and may not be appropriate for patients with moderate hepatic impairment [see Warnings and Precautions (5.11)].

2.6 Stopping Treatment

The decision to discontinue therapy with Buprenorphine and Naloxone Sublingual Tablets after a period of maintenance should be made as part of a comprehensive treatment plan. Both gradual and abrupt discontinuation of buprenorphine has been used, but the data are insufficient to determine the best method of dose taper at the end of treatment.

2.7 Switching Between Buprenorphine and Naloxone Sublingual Film and Buprenorphine and Naloxone Sublingual Tablets

Patients being switched between Buprenorphine and Naloxone Sublingual Tablets and buprenorphine and naloxone sublingual film should be started on the same dosage as the previously administered product. However, dosage adjustments may be necessary when switching between products. Because of the potentially greater relative bioavailability of buprenorphine and naloxone sublingual film compared to Buprenorphine and Naloxone Sublingual Tablets, patients switching from Buprenorphine and Naloxone Sublingual Tablets to buprenorphine and naloxone sublingual film should be monitored for over-medication. Those switching from buprenorphine and naloxone sublingual film to Buprenorphine and Naloxone Sublingual Tablets should be monitored for withdrawal or other indications of under-dosing. In clinical studies, pharmacokinetics of buprenorphine and naloxone sublingual film was similar to the respective dosage strengths of Buprenorphine and Naloxone Sublingual Tablets, although not all doses and dose combinations met bioequivalence criteria.

3 DOSAGE FORMS AND STRENGTHS

Buprenorphine and Naloxone Sublingual Tablets are supplied as an uncoated, round, white, biconvex tablet in two dosage strengths:

- buprenorphine/naloxone 2 mg/0.5 mg, and
- buprenorphine/naloxone 8 mg/2 mg

4 CONTRAINDICATIONS

Buprenorphine and Naloxone Sublingual Tablets should not be administered to patients who have been shown to be hypersensitive to buprenorphine or naloxone as serious adverse reactions, including anaphylactic shock, have been reported [see Warnings and Precautions (5.8)].

5 WARNINGS AND PRECAUTIONS

5.1 Abuse Potential

Buprenorphine can be abused in a manner similar to other opioids, legal or illicit. Prescribe and dispense buprenorphine with appropriate precautions to minimize risk of misuse, abuse, or diversion, and ensure appropriate protection from theft, including in the home. Clinical monitoring appropriate to the patient’s level of stability is essential. Multiple refills should not be prescribed early in treatment or without appropriate patient follow-up visits [see Drug Abuse and Dependence (9.2)].

5.2 Respiratory Depression

Buprenorphine, particularly when taken by the IV route, in combination with benzodiazepines or other CNS depressants (including alcohol), has been associated with significant respiratory depression and death. Many, but not all, post-marketing reports regarding coma and death associated with the concomitant use of buprenorphine and benzodiazepines involved misuse by self-injection. Deaths have also been reported in association with concomitant administration of buprenorphine with other depressants such as alcohol or other CNS depressant drugs. Patients should be warned of the potential danger of self-administration of benzodiazepines or other depressants while under treatment with Buprenorphine and Naloxone Sublingual Tablets [see Drug Interactions (7.3)].

In the case of overdose, the primary management should be the re-establishment of adequate ventilation with mechanical assistance of respiration, if required. Naloxone may be of value for the management of buprenorphine overdose. Higher than normal doses and repeated administration may be necessary.

Buprenorphine and Naloxone Sublingual Tablets should be used with caution in patients with compromised respiratory function (e.g., chronic obstructive pulmonary disease, cor pulmonale, decreased respiratory reserve, hypoxia, hypercapnia, or pre-existing respiratory depression).

5.3 CNS Depression

Patients receiving buprenorphine in the presence of opioid analgesics, general anesthetics, benzodiazepines, phenothiazines, other tranquilizers, sedative/hypnotics, or other CNS depressants (including alcohol) may exhibit increased CNS depression. Consider dose reduction of CNS depressants, Buprenorphine and Naloxone Sublingual Tablets, or both in situations of concomitant prescription [see Drug Interactions (7.3)].

5.4 Unintentional Pediatric Exposure

Buprenorphine can cause severe, possibly fatal, respiratory depression in children who are accidentally exposed to it. Store buprenorphine-containing medications safely out of the sight and reach of children and destroy any unused medication appropriately [see Disposal of Unused Buprenorphine and Naloxone Sublingual Tablets (17)].

5.5 Neonatal Opioid Withdrawal Syndrome

Neonatal opioid withdrawal syndrome (NOWS) is an expected and treatable outcome of prolonged use of opioids during pregnancy, whether that use is medically-authorized or illicit. Unlike opioid withdrawal syndrome in adults, NOWS may be life-threatening if not recognized and treated in the neonate. Healthcare professionals should observe newborns for signs of NOWS and manage accordingly [see Use in Specific Populations (8.1)].

Advise pregnant women receiving opioid addiction treatment with Buprenorphine and Naloxone Sublingual Tablets of the risk of neonatal opioid withdrawal syndrome and ensure that appropriate treatment will be available [see Use in Specific Populations (8.1)]. This risk must be balanced against the risk of untreated opioid addiction which often results in continued or relapsing illicit opioid use and is associated with poor pregnancy outcomes. Therefore, prescribers should discuss the importance and benefits of management of opioid addiction throughout pregnancy.

5.6 Adrenal Insufficiency

Cases of adrenal insufficiency have been reported with opioid use, more often following greater than one month of use. Presentation of adrenal insufficiency may include non-specific symptoms and signs including nausea, vomiting, anorexia, fatigue, weakness, dizziness, and low blood pressure. If adrenal insufficiency is suspected, confirm the diagnosis with diagnostic testing as soon as possible. If adrenal insufficiency is diagnosed, treat with physiologic replacement doses of corticosteroids. Wean the patient off of the opioid to allow adrenal function to recover and continue corticosteroid treatment until adrenal function recovers. Other opioids may be tried as some cases reported use of a different opioid without recurrence of adrenal insufficiency. The information available does not identify any particular opioids as being more likely to be associated with adrenal insufficiency

5.7 Dependence

Buprenorphine is a partial agonist at the mu-opioid receptor and chronic administration produces physical dependence of the opioid type, characterized by withdrawal signs and symptoms upon abrupt discontinuation or rapid taper. The withdrawal syndrome is typically milder than seen with full agonists and may be delayed in onset. Buprenorphine can be abused in a manner similar to other opioids. This should be considered when prescribing or dispensing buprenorphine in situations when the clinician is concerned about an increased risk of misuse, abuse, or diversion [see Drug Abuse and Dependence (9.3)].

5.8 Hepatitis, Hepatic Events

Cases of cytolytic hepatitis and hepatitis with jaundice have been observed in individuals receiving buprenorphine in clinical trials and through post-marketing adverse event reports. The spectrum of abnormalities ranges from transient asymptomatic elevations in hepatic transaminases to case reports of death, hepatic failure, hepatic necrosis, hepatorenal syndrome, and hepatic encephalopathy. In many cases, the presence of pre-existing liver enzyme abnormalities, infection with hepatitis B or hepatitis C virus, concomitant usage of other potentially hepatotoxic drugs, and ongoing injecting drug use may have played a causative or contributory role. In other cases, insufficient data were available to determine the etiology of the abnormality. Withdrawal of buprenorphine has resulted in amelioration of acute hepatitis in some cases; however, in other cases no dose reduction was necessary. The possibility exists that buprenorphine had a causative or contributory role in the development of the hepatic abnormality in some cases. Liver function tests, prior to initiation of treatment is recommended to establish a baseline. Periodic monitoring of liver function during treatment is also recommended. A biological and etiological evaluation is recommended when a hepatic event is suspected. Depending on the case, Buprenorphine and Naloxone Sublingual Tablets may need to be carefully discontinued to prevent withdrawal signs and symptoms and a return by the patient to illicit drug use, and strict monitoring of the patient should be initiated.

5.9 Allergic Reactions

Cases of hypersensitivity to buprenorphine and naloxone-containing products have been reported both in clinical trials and in the post-marketing experience. Cases of bronchospasm, angioneurotic edema, and anaphylactic shock have been reported. The most common signs and symptoms include rashes, hives, and pruritus. A history of hypersensitivity to buprenorphine or naloxone is a contraindication to the use of Buprenorphine and Naloxone Sublingual Tablets.

5.10 Precipitation of Opioid Withdrawal Signs and Symptoms

Because it contains naloxone, Buprenorphine and Naloxone Sublingual Tablets are highly likely to produce marked and intense withdrawal signs and symptoms if misused parenterally by individuals dependent on full opioid agonists such as heroin, morphine, or methadone. Because of the partial agonist properties of buprenorphine, Buprenorphine and Naloxone Sublingual Tablets may precipitate opioid withdrawal signs and symptoms in such persons if administered sublingually before the agonist effects of the opioid have subsided.

5.11 Use in Opioid Naïve Patients

There have been reported deaths of opioid naïve individuals who received a 2 mg dose of buprenorphine as a sublingual tablet for analgesia. Buprenorphine and Naloxone Sublingual Tablets are not appropriate as an analgesic.

5.12 Use in Patients With Impaired Hepatic Function

Buprenorphine/ naloxone products are not recommended in patients with severe hepatic impairment and may not be appropriate for patients with moderate hepatic impairment. The doses of buprenorphine and naloxone in this fixed-dose combination product cannot be individually titrated, and hepatic impairment results in a reduced clearance of naloxone to a much greater extent than buprenorphine. Therefore, patients with severe hepatic impairment will be exposed to substantially higher levels of naloxone than patients with normal hepatic function. This may interfere with buprenorphine’s efficacy throughout treatment. In patients with moderate hepatic impairment, the differential reduction of naloxone clearance compared to buprenorphine clearance is not as great as in subjects with severe hepatic impairment. Therefore, buprenorphine/naloxone products may be used with caution for maintenance treatment in patients with moderate hepatic impairment who have initiated treatment on a buprenorphine product without naloxone. However, patients should be carefully monitored and consideration given to the possibility of naloxone interfering with buprenorphine’s efficacy [see Use in Specific Populations (8.6)].

5.13 Impairment of Ability to Drive or Operate Machinery

Buprenorphine and Naloxone Sublingual Tablets may impair the mental or physical abilities required for the performance of potentially dangerous tasks such as driving a car or operating machinery, especially during treatment induction and dose adjustment. Patients should be cautioned about driving or operating hazardous machinery until they are reasonably certain that Buprenorphine and Naloxone Sublingual Tablet therapy does not adversely affect his or her ability to engage in such activities.

5.14 Orthostatic Hypotension

Like other opioids, Buprenorphine and Naloxone Sublingual Tablets may produce orthostatic hypotension in ambulatory patients.

5.15 Elevation of Cerebrospinal Fluid Pressure

Buprenorphine, like other opioids, may elevate cerebrospinal fluid pressure and should be used with caution in patients with head injury, intracranial lesions, and other circumstances when cerebrospinal pressure may be increased. Buprenorphine can produce miosis and changes in the level of consciousness that may interfere with patient evaluation.

5.16 Elevation of Intracholedochal Pressure

Buprenorphine has been shown to increase intracholedochal pressure, as do other opioids, and thus should be administered with caution to patients with dysfunction of the biliary tract.

5.17 Effects in Acute Abdominal Conditions

As with other opioids, buprenorphine may obscure the diagnosis or clinical course of patients with acute abdominal conditions.

5.18 General Precautions

Buprenorphine and Naloxone Sublingual Tablets should be administered with caution in debilitated patients and those with myxedema or hypothyroidism, adrenal cortical insufficiency (e.g., Addison's disease); CNS depression or coma; toxic psychoses; prostatic hypertrophy or urethral stricture; acute alcoholism; delirium tremens; or kyphoscoliosis.

6 ADVERSE REACTIONS

Because clinical trials are conducted under widely varying conditions, adverse reaction rates observed in the clinical trials of a drug cannot be directly compared to rates in the clinical trials of another drug and may not reflect the rates observed in practice.

6.1 Adverse Events in Clinical Trials - Buprenorphine and Naloxone Sublingual Tablets

The safety of Buprenorphine and Naloxone Sublingual Tablets was evaluated in 497 opioid-dependent subjects. The prospective evaluation of Buprenorphine and Naloxone Sublingual Tablets were supported by clinical trials using buprenorphine sublingual tablets and other trials using buprenorphine sublingual solutions. In total, safety data were available from 3214 opioid-dependent subjects exposed to buprenorphine at doses in the range used in treatment of opioid addiction.

Few differences in adverse event profile were noted between Buprenorphine and Naloxone Sublingual Tablets and buprenorphine sublingual tablets or buprenorphine administered as a sublingual solution.

The following adverse events were reported to occur by at least 5% of patients in a 4-week study (Table 1).

Table 1. Adverse Events (≥ 5%) by Body System and Treatment Group in a 4-week Study
Body System / Adverse Event (COSTART Terminology) | N (%) Buprenorphine and Naloxone Sublingual Tablets 16 mg/day N=107 | N (%) Placebo N=107
Body as a Whole
Asthenia | 7 (6.5%) | 7 (6.5%)
Chills | 8 (7.5%) | 8 (7.5%)
Headache | 39 (36.4%) | 24 (22.4%)
Infection | 6 (5.6%) | 7 (6.5%)
Pain | 24 (22.4%) | 20 (18.7%)
Pain Abdomen | 12 (11.2%) | 7 (6.5%)
Pain Back | 4 (3.7%) | 12 (11.2%)
Withdrawal Syndrome | 27 (25.2%) | 40 (37.4%)
Cardiovascular System
Vasodilation | 10 (9.3%) | 7 (6.5%)
Digestive System
Constipation | 13 (12.1%) | 3 (2.8%)
Diarrhea | 4 (3.7%) | 16 (15.0%)
Nausea | 16 (15.0%) | 12 (11.2%)
Vomiting | 8 (7.5%) | 5 (4.7%)
Nervous System
Insomnia | 15 (14.0%) | 17 (15.9%)
Respiratory System
Rhinitis | 5 (4.7%) | 14 (13.1%)
Skin And Appendages
Sweating | 15 (14.0%) | 11 (10.3%)

The adverse event profile of buprenorphine was also characterized in the dose-controlled study of buprenorphine solution, over a range of doses in four months of treatment. Table 2 shows adverse events reported by at least 5% of subjects in any dose group in the dose-controlled study.

Table 2. Adverse Events (≥ 5%) by Body System and Treatment Group in a 16-Week Study
Body System /Adverse Event (COSTART Terminology) | Buprenorphine Dose*
Body System /Adverse Event (COSTART Terminology) | Very Low* (N=184) | Low* (N=180) | Moderate* (N=186) | High* (N=181) | Total* (N=731)
Body System /Adverse Event (COSTART Terminology) | N (%) | N (%) | N (%) | N (%) | N (%)
*Sublingual solution. Doses in this table cannot necessarily be delivered in tablet form, but for comparison purposes:
"Very low" dose (1 mg solution) would be less than a tablet dose of 2 mg
"Low" dose (4 mg solution) approximates a 6 mg tablet dose
"Moderate" dose (8 mg solution) approximates a 12 mg tablet dose
"High" dose (16 mg solution) approximates a 24 mg tablet dose
Body as a Whole
Abscess | 9 (5%) | 2 (1%) | 3 (2%) | 2 (1%) | 16 (2%)
Asthenia | 26 (14%) | 28 (16%) | 26 (14%) | 24 (13%) | 104 (14%)
Chills | 11 (6%) | 12 (7%) | 9 (5%) | 10 (6%) | 42 (6%)
Fever | 7 (4%) | 2 (1%) | 2 (1%) | 10 (6%) | 21 (3%)
Flu Syndrome | 4 (2%) | 13 (7%) | 19 (10%) | 8 (4%) | 44 (6%)
Headache | 51 (28%) | 62 (34%) | 54 (29%) | 53 (29%) | 220 (30%)
Infection | 32 (17%) | 39 (22%) | 38 (20%) | 40 (22%) | 149 (20%)
Injury Accidental | 5 (3%) | 10 (6%) | 5 (3%) | 5 (3%) | 25 (3%)
Pain | 47 (26%) | 37 (21%) | 49 (26%) | 44 (24%) | 177 (24%)
Pain Back | 18 (10%) | 29 (16%) | 28 (15%) | 27 (15%) | 102 (14%)
Withdrawal Syndrome | 45 (24%) | 40 (22%) | 41 (22%) | 36 (20%) | 162 (22%)
Digestive System
Constipation | 10 (5%) | 23 (13%) | 23 (12%) | 26 (14%) | 82 (11%)
Diarrhea | 19 (10%) | 8 (4%) | 9 (5%) | 4 (2%) | 40 (5%)
Dyspepsia | 6 (3%) | 10 (6%) | 4 (2%) | 4 (2%) | 24 (3%)
Nausea | 12 (7%) | 22 (12%) | 23 (12%) | 18 (10%) | 75 (10%)
Vomiting | 8 (4%) | 6 (3%) | 10 (5%) | 14 (8%) | 38 (5%)
Nervous System
Anxiety | 22 (12%) | 24 (13%) | 20 (11%) | 25 (14%) | 91 (12%)
Depression | 24 (13%) | 16 (9%) | 25 (13%) | 18 (10%) | 83 (11%)
Dizziness | 4 (2%) | 9 (5%) | 7 (4%) | 11 (6%) | 31 (4%)
Insomnia | 42 (23%) | 50 (28%) | 43 (23%) | 51 (28%) | 186 (25%)
Nervousness | 12 (7%) | 11 (6%) | 10 (5%) | 13 (7%) | 46 (6%)
Somnolence | 5 (3%) | 13 (7%) | 9 (5%) | 11 (6%) | 38 (5%)
Respiratory System
Cough Increase | 5 (3%) | 11 (6%) | 6 (3%) | 4 (2%) | 26 (4%)
Pharyngitis | 6 (3%) | 7 (4%) | 6 (3%) | 9 (5%) | 28 (4%)
Rhinitis | 27 (15%) | 16 (9%) | 15 (8%) | 21 (12%) | 79 (11%)
Skin And Appendages
Sweat | 23 (13%) | 21 (12%) | 20 (11%) | 23 (13%) | 87 (12%)
Special Senses
Runny Eyes | 13 (7%) | 9 (5%) | 6 (3%) | 6 (3%) | 34 (5%)

6.2 Adverse Events – Post-marketing Experience with Buprenorphine and Naloxone Sublingual Tablets

The most frequently reported post-marketing adverse event not observed in clinical trials was peripheral edema.

Serotonin syndrome: Cases of serotonin syndrome, a potentially life-threatening condition, have been reported during concomitant use of opioids with serotonergic drugs.

Adrenal insufficiency: Cases of adrenal insufficiency have been reported with opioid use, more often following greater than one month of use.

Anaphylaxis: Anaphylaxis has been reported with ingredients contained in Buprenorphine and Naloxone Sublingual Tablets.

Androgen deficiency: Cases of androgen deficiency have occurred with chronic use of opioids [See Clinical Pharmacology (12.2)].

7 DRUG INTERACTIONS

7.1 Cytochrome P-450 3A4 (CYP3A4) Inhibitors and Inducers

Buprenorphine is metabolized to norbuprenorphine primarily by cytochrome CYP3A4; therefore, potential interactions may occur when Buprenorphine and Naloxone Sublingual Tablets are given concurrently with agents that affect CYP3A4 activity. The concomitant use of Buprenorphine and Naloxone Sublingual Tablets with CYP3A4 inhibitors (e.g., azole antifungals such as ketoconazole, macrolide antibiotics such as erythromycin, and HIV protease inhibitors) should be monitored and may require dose-reduction of one or both agents.

The interaction of buprenorphine with CYP3A4 inducers has not been studied; therefore, it is recommended that patients receiving Buprenorphine and Naloxone Sublingual Tablets be monitored for signs and symptoms of opioid withdrawal if inducers of CYP3A4 (e.g., efavirenz, phenobarbital, carbamazepine, phenytoin, rifampicin) are co-administered [see Clinical Pharmacology (12.3)].

7.2 Antiretrovirals

Three classes of antiretroviral agents have been evaluated for CYP3A4 interactions with buprenorphine. Nucleoside reverse transcriptase inhibitors (NRTIs) do not appear to induce or inhibit the P450 enzyme pathway, thus no interactions with buprenorphine are expected. Non-nucleoside reverse transcriptase inhibitors (NNRTIs) are metabolized principally by CYP3A4. Efavirenz, nevirapine and etravirine are known CYP3A inducers whereas delaviridine is a CYP3A inhibitor. Significant pharmacokinetic interactions between NNRTIs (e.g., efavirenz and delavirdine) and buprenorphine have been shown in clinical studies, but these pharmacokinetic interactions did not result in any significant pharmacodynamic effects. It is recommended that patients who are on chronic buprenorphine treatment have their dose monitored if NNRTIs are added to their treatment regimen. Studies have shown some antiretroviral protease inhibitors (PIs) with CYP3A4 inhibitory activity (nelfinavir, lopinavir/ritonavir, ritonavir) have little effect on buprenorphine pharmacokinetic and no significant pharmacodynamic effects. Other PIs with CYP3A4 inhibitory activity (atazanavir and atazanavir/ritonavir) resulted in elevated levels of buprenorphine and norbuprenorphine and patients in one study reported increased sedation. Symptoms of opioid excess have been found in post-marketing reports of patients receiving buprenorphine and atazanavir with and without ritonavir concomitantly. Monitoring of patients taking buprenorphine and atazanavir with and without ritonavir is recommended, and dose reduction of buprenorphine may be warranted.

7.3 Benzodiazepines

There have been a number of post-marketing reports regarding coma and death associated with the concomitant use of buprenorphine and benzodiazepines. In many, but not all of these cases, buprenorphine was misused by self-injection. Preclinical studies have shown that the combination of benzodiazepines and buprenorphine altered the usual ceiling effect on buprenorphine-induced respiratory depression, making the respiratory effects of buprenorphine appear similar to those of full opioid agonists. Buprenorphine and Naloxone Sublingual Tablets should be prescribed with caution to patients taking benzodiazepines or other drugs that act on the CNS, regardless of whether these drugs are taken on the advice of a physician or are being abused/misused. Patients should be warned that it is extremely dangerous to self-administer non-prescribed benzodiazepines while taking Buprenorphine and Naloxone Sublingual Tablets, and should also be cautioned to use benzodiazepines concurrently with Buprenorphine and Naloxone Sublingual Tablets only as directed by their physician.

7.4 Serotonergic Drugs

The concomitant use of opioids with other drugs that affect the serotonergic neurotransmitter system, such as selective serotonin reuptake inhibitors (SSRIs), serotonin and norepinephrine reuptake inhibitors (SNRIs), tricyclic antidepressants (TCAs), triptans, 5-HT3 receptor antagonists, drugs that effect the serotonin neurotransmitter system (e.g., mirtazapine, trazodone, tramadol), and monoamine oxidase (MAO) inhibitors (those intended to treat psychiatric disorders and also others, such as linezolid and intravenous methylene blue), has resulted in serotonin syndrome.

If concomitant use is warranted, carefully observe the patient, particularly during treatment initiation and dose adjustment. Discontinue Buprenorphine and Naloxone Sublingual Tablets if serotonin syndrome is suspected.

8 USE IN SPECIFIC POPULATIONS

8.1 Pregnancy

Pregnancy Category C.

Risk Summary

There are no adequate and well-controlled studies of Buprenorphine and Naloxone Sublingual Tablets or buprenorphine/naloxone in pregnant women. Limited published data on use of buprenorphine, the active ingredient in of Buprenorphine and Naloxone Sublingual Tablets, in pregnancy, have not shown an increased risk of major malformations. All pregnancies, regardless of drug exposure, have a background risk of 2 to 4% for major birth defects, and 15 to 20% for pregnancy loss. Reproductive and developmental studies in rats and rabbits identified adverse events at clinically relevant doses. Pre-and postnatal development studies in rats demonstrated dystocia, increased neonatal deaths, and developmental delays. No clear teratogenic effects were seen with a range of doses equivalent to or greater than the human dose. However, in a few studies, some events such as acephalus, omphalocele, and skeletal abnormalities were observed but these findings were not clearly treatment-related. Embryofetal death was also observed in both rats and rabbits

Buprenorphine and Naloxone Sublingual Tablets should be used during pregnancy only if the potential benefit justifies the potential risk to the fetus.

Clinical Considerations

Disease-associated maternal and embryo-fetal risk

Untreated opioid addition in pregnancy is associated with adverse obstetrical outcomes such as low birth weight, preterm birth, and fetal death. In addition, untreated opioid addiction often results in continued or relapsing illicit opioid use.

Fetal/neonatal adverse reactions

Neonatal opioid withdrawal syndrome may occur in newborn infants of mothers who are receiving treatment with Buprenorphine and Naloxone Sublingual Tablets.

Neonatal opioid withdrawal syndrome presents as irritability, hyperactivity and abnormal sleep pattern, high pitched cry, tremors, vomiting, diarrhea and/or failure to gain weight. Signs of neonatal withdrawal usually occur in the first days after birth. The duration and severity of neonatal opioid withdrawal syndrome may vary. Observe newborns for signs of neonatal opioid withdrawal syndrome and manage accordingly [see Warnings and Precautions (5.5)].

Labor or Delivery

As with all opioids, use of buprenorphine prior to delivery may result in respiratory depression in the newborn. Closely monitor neonates for signs of respiratory depression. An opioid antagonist such as naloxone should be available for reversal of opioid induced respiratory depression in the neonate.

Data

Human Data

Studies have been conducted to evaluate neonatal outcomes in women exposed to buprenorphine during pregnancy. Limited published data on malformations from trials, observational studies, case series, and case reports on buprenorphine use in pregnancy have not shown an increased risk of major malformations. Based on these studies the incidence of neonatal abstinence syndrome is not clear and there does not appear to be a dose-response relationship.

Animal Data

Effects on embryo-fetal development were studied in Sprague-Dawley rats and Russian white rabbits following oral (1:1) and intramuscular (IM) (3:2) administration of mixtures of buprenorphine and naloxone. Following oral administration to rats and rabbits, no teratogenic effects were observed at buprenorphine doses up to 250 mg/kg/day and 40 mg/kg/day, respectively (estimated exposure approximately 150 times and 50 times, respectively, the recommended human daily sublingual dose of 16 mg on a mg/m^2 basis). No definitive drug-related teratogenic effects were observed in rats and rabbits at IM doses up to 30 mg/kg/day (estimated exposure approximately 20 times and 35 times, respectively, the recommended human daily dose of 16 mg on a mg/m^2 basis). Acephalus was observed in one rabbit fetus from the low-dose group and omphalocele was observed in two rabbit fetuses from the same litter in the mid-dose group; no findings were observed in fetuses from the high-dose group. Following oral administration of buprenorphine to rats, dose-related post-implantation losses, evidenced by increases in the numbers of early resorptions with consequent reductions in the numbers of fetuses, were observed at doses of 10 mg/kg/day or greater (estimated exposure approximately 6 times the recommended human daily sublingual dose of 16 mg on a mg/m^2 basis). In the rabbit, increased post-implantation losses occurred at an oral dose of 40 mg/kg/day. Following IM administration in the rat and the rabbit, post-implantation losses, as evidenced by decreases in live fetuses and increases in resorptions, occurred at 30 mg/kg/day.

Buprenorphine was not teratogenic in rats or rabbits after IM or subcutaneous (SC) doses up to 5 mg/kg/day (estimated exposure was approximately 3 and 6 times, respectively, the recommended human daily sublingual dose of 16 mg on a mg/m^2 basis), after IV doses up to 0.8 mg/kg/day (estimated exposure was approximately 0.5 times and equal to, respectively, the recommended human daily sublingual dose of 16 mg on a mg/m^2 basis), or after oral doses up to 160 mg/kg/day in rats (estimated exposure was approximately 95 times the recommended human daily sublingual dose of 16 mg on a mg/m^2 basis) and 25 mg/kg/day in rabbits (estimated exposure was approximately 30 times the recommended human daily sublingual dose of 16 mg on a mg/m^2 basis). Significant increases in skeletal abnormalities (e.g., extra thoracic vertebra or thoraco-lumbar ribs) were noted in rats after SC administration of 1 mg/kg/day and up (estimated exposure was approximately 0.6 times the recommended human daily sublingual dose of 16 mg on a mg/m^2 basis), but were not observed at oral doses up to 160 mg/kg/day. Increases in skeletal abnormalities in rabbits after IM administration of 5 mg/kg/day (estimated exposure was approximately 6 times the recommended human daily sublingual dose of 16 mg on a mg/m^2 basis) or oral administration of 1 mg/kg/day or greater (estimated exposure was approximately equal to the recommended human daily sublingual dose of 16 mg on a mg/m^2 basis) were not statistically significant.

In rabbits, buprenorphine produced statistically significant pre-implantation losses at oral doses of 1 mg/kg/day or greater and post-implantation losses that were statistically significant at IV doses of 0.2 mg/kg/day or greater (estimated exposure approximately 0.3 times the recommended human daily sublingual dose of 16 mg on a mg/m^2 basis).

Dystocia was noted in pregnant rats treated intramuscularly with buprenorphine 5 mg/kg/day (approximately 3 times the recommended human daily sublingual dose of 16 mg on a mg/m^2 basis). Fertility, peri-, and postnatal development studies with buprenorphine in rats indicated increases in neonatal mortality after oral doses of 0.8 mg/kg/day and up (approximately 0.5 times the recommended human daily sublingual dose of 16 mg on a mg/m^2 basis), after IM doses of 0.5 mg/kg/day and up (approximately 0.3 times the recommended human daily sublingual dose of 16 mg on a mg/m^2 basis), and after SC doses of 0.1 mg/kg/day and up (approximately 0.06 times the recommended human daily sublingual dose of 16 mg on a mg/m^2 basis). An apparent lack of milk production during these studies likely contributed to the decreased pup viability and lactation indices. Delays in the occurrence of righting reflex and startle response were noted in rat pups at an oral dose of 80 mg/kg/day (approximately 50 times the recommended human daily sublingual dose of 16 mg on a mg/m^2 basis).

8.3 Nursing Mothers

Risk Summary

Based on two studies in 13 lactating women, buprenorphine and its metabolite norbuprenorphine are present in low levels in human milk and infant urine, and available data have not shown adverse reactions in breastfed infants. There are no data on the combination product buprenorphine/naloxone in breastfeeding, however oral absorption of naloxone is minimal. Caution should be exercised when Buprenorphine and Naloxone Sublingual Tablets are administered to a nursing woman. The developmental and health benefits of breastfeeding should be considered along with the mother’s clinical need for buprenorphine and naloxone and any potential adverse effects on the breastfed child from the drug or from the underlying maternal condition.

Clinical Considerations

Advise the nursing mother taking Buprenorphine and Naloxone Sublingual Tablets to monitor the infant for increased drowsiness and breathing difficulties.

Data

Based on limited data from a study of 6 lactating women who were taking a median oral dose of buprenorphine of 0.29 mg/kg/day 5 to 8 days after delivery, breast milk contained a median infant dose of 0.42 mcg/kg/day of buprenorphine and 0.33 mcg/kg/day of norbuprenorphine, which are equal to 0.2% and 0.12% of the maternal weight-adjusted dose.

Based on limited data from a study of 7 lactating women who were taking a median oral dose of buprenorphine of 7 mg/day an average of 1.12 months after delivery, the mean milk concentrations of buprenorphine and norbuprenorphine were 3.65 mcg/L and 1.94 mcg/L respectively. Based on the limited data from this study, and assuming milk consumption of 150 mL/kg/day, an exclusively breastfed infant would receive an estimated mean of 0.55 mcg/kg/day of buprenorphine and 0.29 mcg/kg/day of norbuprenorphine, which are 0.38% and 0.18% of the maternal weight-adjusted dose.

No adverse reactions were observed in the infants in these two studies.

Females and Males Reproductive Potential

Infertility
Chronic use of opioids may cause reduced fertility in females and males of reproductive potential. It is not known whether these effects on fertility are reversible [see Adverse Reactions (6.2)].

8.4 Pediatric Use

The safety and effectiveness of Buprenorphine and Naloxone Sublingual Tablets have not been established in pediatric patients. This product is not appropriate for the treatment of neonatal abstinence syndrome in neonates, because it contains naloxone, an opioid antagonist.

8.5 Geriatric Use

Clinical studies of Buprenorphine and Naloxone Sublingual Tablets, buprenorphine and naloxone sublingual film, or buprenorphine sublingual tablets did not include sufficient numbers of subjects aged 65 and over to determine whether they responded differently than younger subjects. Other reported clinical experience has not identified differences in responses between the elderly and younger patients. In general, dose selection for an elderly patient should be cautious, usually starting at the low end of the dosing range, reflecting the greater frequency of decreased hepatic, renal, or cardiac function, and of concomitant disease or other drug therapy.

8.6 Hepatic Impairment

The effect of hepatic impairment on the pharmacokinetics of buprenorphine and naloxone has been evaluated in a pharmacokinetic study. Both drugs are extensively metabolized in the liver. While no clinically significant changes have been observed in subjects with mild hepatic impairment; the plasma levels have been shown to be higher and half-life values have been shown to be longer for both buprenorphine and naloxone in subjects with moderate and severe hepatic impairment. The magnitude of the effects on naloxone are greater than that on buprenorphine in both moderately and severely impaired subjects. The difference in magnitude of the effects on naloxone and buprenorphine are greater in subjects with severe hepatic impairment than in subjects with moderate hepatic impairment, and therefore the clinical impact of these effects is likely to be greater in patients with severe hepatic impairment than in patients with moderate hepatic impairment. Buprenorphine/naloxone products should be avoided in patients with severe hepatic impairment and may not be appropriate for patients with moderate hepatic impairment [see Warnings and Precautions (5.11), and Clinical Pharmacology (12.3)].

8.7 Renal Impairment

No differences in buprenorphine pharmacokinetics were observed between 9 dialysis-dependent and 6 normal patients following IV administration of 0.3 mg buprenorphine. The effects of renal failure on naloxone pharmacokinetics are unknown.

9 DRUG ABUSE AND DEPENDENCE

9.1 Controlled Substance

Buprenorphine is a Schedule III narcotic under the Controlled Substances Act.

Under the Drug Addiction Treatment Act (DATA) codified at 21 U.S.C. 823(g), prescription use of this product in the treatment of opioid dependence is limited to physicians who meet certain qualifying requirements, and who have notified the Secretary of Health and Human Services (HHS) of their intent to prescribe this product for the treatment of opioid dependence and have been assigned a unique identification number that must be included on every prescription.

9.2 Abuse

Buprenorphine, like morphine and other opioids, has the potential for being abused and is subject to criminal diversion. This should be considered when prescribing or dispensing buprenorphine in situations when the clinician is concerned about an increased risk of misuse, abuse, or diversion. Healthcare professionals should contact their state professional licensing board or state controlled substances authority for information on how to prevent and detect abuse or diversion of this product.

Patients who continue to misuse, abuse, or divert buprenorphine products or other opioids should be provided with, or referred to, more intensive and structured treatment.

Abuse of buprenorphine poses a risk of overdose and death. This risk is increased with the abuse of buprenorphine and alcohol and other substances, especially benzodiazepines.

The physician may be able to more easily detect misuse or diversion by maintaining records of medication prescribed including date, dose, quantity, frequency of refills, and renewal requests of medication prescribed.

Proper assessment of the patient, proper prescribing practices, periodic re-evaluation of therapy, and proper handling and storage of the medication are appropriate measures that help to limit abuse of opioid drugs.

9.3 Dependence

Buprenorphine is a partial agonist at the mu-opioid receptor and chronic administration produces physical dependence of the opioid type, characterized by moderate withdrawal signs and symptoms upon abrupt discontinuation or rapid taper. The withdrawal syndrome is typically milder than seen with full agonists and may be delayed in onset [see Warnings and Precautions (5.6)].

Neonatal opioid withdrawal syndrome (NOWS) is an expected and treatable outcome of prolonged use of opioids during pregnancy [see Warnings and Precautions (5.5)].

10 OVERDOSAGE

The manifestations of acute overdose include pinpoint pupils, sedation, hypotension, respiratory depression, and death.

In the event of overdose, the respiratory and cardiac status of the patient should be monitored carefully. When respiratory or cardiac functions are depressed, primary attention should be given to the re-establishment of adequate respiratory exchange through provision of a patent airway and institution of assisted or controlled ventilation. Oxygen, IV fluids, vasopressors, and other supportive measures should be employed as indicated.

In the case of overdose, the primary management should be the reestablishment of adequate ventilation with mechanical assistance of respiration, if required. Naloxone may be of value for the management of buprenorphine overdose. Higher than normal doses and repeated administration may be necessary. The long duration of action of buprenorphine and naloxone should be taken into consideration when determining the length of treatment and medical surveillance needed to reverse the effects of an overdose. Insufficient duration of monitoring may put patients at risk.

11 DESCRIPTION

Buprenorphine and Naloxone Sublingual Tablets are uncoated, round, white tablet with “↑” on one side and an “N2” or “N8” debossed on the other side. “N2” indicating the 2 mg/0.5 mg strength and the “N8” indicating the 8 mg/2 mg strength. They contain buprenorphine HCl, a mu-opioid receptor partial agonist and a kappa-opioid receptor antagonist, and naloxone HCl dihydrate, an opioid receptor antagonist, at a ratio of 4:1 (ratio of free bases). It is intended for sublingual administration and is available in two dosage strengths, 2 mg buprenorphine with 0.5 mg naloxone and 8 mg buprenorphine with 2 mg naloxone. Each sublingual tablet also contains lactose monohydrate, mannitol, cornstarch, povidone, purified water, citric acid anhydrous, sodium citrate, sodium stearyl fumarate, acesulfame K sweetener, a lemon flavor and a lime flavor.

Chemically, buprenorphine HCl is (2S)-2-[17-Cyclopropylmethyl-4,5α-epoxy-3-hydroxy-6-methoxy-6α,14-ethano-14α-morphinan-7α-yl]-3,3dimethylbutan-2-ol hydrochloride. It has the following chemical structure:

Buprenorphine HCl has the molecular formula C29 H41 NO4 • HCl and the molecular weight is 504.10. It is a white or off-white crystalline powder, sparingly soluble in water, freely soluble in methanol, soluble in alcohol, and practically insoluble in cyclohexane.

Chemically, naloxone HCl dihydrate is 17-Allyl-4, 5 α-epoxy-3, 14-dihydroxymorphinan-6-one hydrochloride dihydrate. It has the following chemical structure:

Naloxone hydrochloride dihydrate has the molecular formula C19H21NO4 • HCl • 2H20 and the molecular weight is 399.87. It is a white to slightly off-white powder and is freely soluble in water, soluble in alcohol, and practically insoluble in toluene and ether.

12 CLINICAL PHARMACOLOGY

12.1 Mechanism of Action

Buprenorphine and Naloxone Sublingual Tablets contains buprenorphine and naloxone. Buprenorphine is a partial agonist at the mu-opioid receptor and an antagonist at the kappa-opioid receptor. Naloxone is a potent antagonist at mu-opioid receptors and produces opioid withdrawal signs and symptoms in individuals physically dependent on full opioid agonists when administered parenterally.

12.2 Pharmacodynamics

Subjective Effects:

Comparisons of buprenorphine to full opioid agonists such as methadone and hydromorphone suggest that sublingual buprenorphine produces typical opioid agonist effects which are limited by a ceiling effect.

In opioid-experienced subjects who were not physically dependent, acute sublingual doses of buprenorphine/naloxone tablets produced opioid agonist effects which reached a maximum between doses of 8 mg/2 mg and 16 mg/4 mg buprenorphine/naloxone.

Opioid agonist ceiling-effects were also observed in a double-blind, parallel group, dose-ranging comparison of single doses of buprenorphine sublingual solution (1, 2, 4, 8, 16, or 32 mg), placebo and a full agonist control at various doses. The treatments were given in ascending dose order at intervals of at least one week to 16 opioid-experienced subjects who were not physically dependent. Both active drugs produced typical opioid agonist effects. For all measures for which the drugs produced an effect, buprenorphine produced a dose-related response. However, in each case, there was a dose that produced no further effect. In contrast, the highest dose of the full agonist control always produced the greatest effects. Agonist objective rating scores remained elevated for the higher doses of buprenorphine (8 to 32 mg) longer than for the lower doses and did not return to baseline until 48 hours after drug administration. The onset of effects appeared more rapidly with buprenorphine than with the full agonist control, with most doses nearing peak effect after 100 minutes for buprenorphine compared to 150 minutes for the full agonist control.

Physiologic Effects:

Buprenorphine in IV (2, 4, 8, 12 and 16 mg) and sublingual (12 mg) doses has been administered to opioid-experienced subjects who were not physically dependent to examine cardiovascular, respiratory, and subjective effects at doses comparable to those used for treatment of opioid dependence. Compared to placebo, there were no statistically significant differences among any of the treatment conditions for blood pressure, heart rate, respiratory rate, O2 saturation, or skin temperature across time. Systolic BP was higher in the 8 mg group than placebo (3-hour AUC values). Minimum and maximum effects were similar across all treatments. Subjects remained responsive to low voice and responded to computer prompts. Some subjects showed irritability, but no other changes were observed.

The respiratory effects of sublingual buprenorphine were compared with the effects of methadone in a double-blind, parallel group, dose ranging comparison of single doses of buprenorphine sublingual solution (1, 2, 4, 8, 16, or 32 mg) and oral methadone (15, 30, 45, or 60 mg) in non-dependent, opioid-experienced volunteers. In this study, hypoventilation not requiring medical intervention was reported more frequently after buprenorphine doses of 4 mg and higher than after methadone. Both drugs decreased O2 saturation to the same degree.

Effect of Naloxone:

Physiologic and subjective effects following acute sublingual administration of buprenorphine tablets and buprenorphine/naloxone tablets were similar at equivalent dose levels of buprenorphine. Naloxone had no clinically significant effect when administered by the sublingual route, although blood levels of the drug were measurable. Buprenorphine/naloxone, when administered sublingually to an opioid-dependent cohort, was recognized as an opioid agonist, whereas when administered intramuscularly, combinations of buprenorphine with naloxone produced opioid antagonist actions similar to naloxone. This finding suggests that the naloxone in buprenorphine/naloxone tablets may deter injection of buprenorphine/naloxone tablets by persons with active substantial heroin or other full mu-opioid dependence. However, clinicians should be aware that some opioid-dependent persons, particularly those with a low level of full mu-opioid physical dependence or those whose opioid physical dependence is predominantly to buprenorphine, abuse buprenorphine and naloxone combinations by the intravenous or intranasal route. In methadone-maintained patients and heroin-dependent subjects, IV administration of buprenorphine/naloxone combinations precipitated opioid withdrawal signs and symptoms and was perceived as unpleasant and dysphoric. In morphine-stabilized subjects, intravenously administered combinations of buprenorphine with naloxone produced opioid antagonist and withdrawal signs and symptoms that were ratio-dependent; the most intense withdrawal signs and symptoms were produced by 2:1 and 4:1 ratios, less intense by an 8:1 ratio.

Effects on the Endocrine System:

Chronic use of opioids may influence the hypothalamic-pituitary-gonodal axis, leading to hormonal changes that may manifest as low libido, impotence, erectile dysfunction, amenorrhea, or infertility. The causal role of opioids in the clinical syndrome of hypogonadism is unknown because the various medical, physical, lifestyle, and psychological stressors that may influence gonadal hormone levels have not been adequately controlled for in studies conducted to date [see Adverse Reactions (6.2)]

12.3 Pharmacokinetics

Absorption:

Plasma levels of buprenorphine and naloxone increased with the sublingual dose of Buprenorphine and Naloxone Sublingual Tablets (Table 3). There was wide inter-patient variability in the sublingual absorption of buprenorphine and naloxone, but within subjects the variability was low. Both Cmax and AUC of buprenorphine increased in a linear fashion with the increase in dose (in the range of 4 to 16 mg), although the increase was not directly dose-proportional.

Naloxone did not affect the pharmacokinetics of buprenorphine and both buprenorphine HCl and naloxone HCl. At the three naloxone doses of 1, 2, and 4 mg, levels above the limit of quantitation (0.05 ng/mL) were not detected beyond 2 hours in seven of eight subjects. In one individual, at the 4 mg dose, the last measurable concentration was at 8 hours. Within each subject (for most of the subjects), across the doses there was a trend toward an increase in naloxone concentrations with increase in dose. Mean peak naloxone levels ranged from 0.11 ng/mL to 0.28 ng/mL in the dose range of 1 mg to 4 mg.

Table 3. Pharmacokinetic Parameters of Buprenorphine, Norbuprenorphine, and Naloxone After the Sublingual Administration of Buprenorphine and Naloxone Sublingual Tablets
Dose | Analyte | Mean SD | Cmax (ng/mL) | Tmax (h) | AUCinf (h•ng/mL) | t1/2 (h)
2 mg/ 0.5 mg | Buprenorphine | Mean SD | 0.947 0.374 | 1.72 0.60 | 8.654 2.854 | 33.41 13.01
2 mg/ 0.5 mg | Norbuprenorphine | Mean SD | 0.312 0.140 | 2.26 2.03 | 14.52 5.776 | 56.09 31.14
2 mg/ 0.5 mg | Naloxone* | Mean SD | 54.1 23.0 | 0.77 0.26 | 137.3 43.10 | 5.00 5.52
8 mg/ 2 mg | Buprenorphine | Mean SD | 3.37 1.80 | 1.53 0.66 | 30.45 13.03 | 32.82 9.81
8 mg/ 2 mg | Norbuprenorphine | Mean SD | 1.40 1.08 | 2.17 2.63 | 54.91 36.01 | 41.96 17.92
8 mg/ 2 mg | Naloxone* | Mean SD | 193 91.2 | 0.81 0.19 | 480.8 201.0 | 6.25 3.14
*Naloxone Cmax expressed as pg/mL. Naloxone AUCinf expressed as h•pg/mL

Distribution:

Buprenorphine is approximately 96% protein bound, primarily to alpha and beta globulin.

Naloxone is approximately 45% protein bound, primarily to albumin.

Metabolism:

Buprenorphine undergoes both N-dealkylation to norbuprenorphine and glucuronidation. The N-dealkylation pathway is mediated primarily by the CYP3A4. Norbuprenorphine, the major metabolite, can further undergo glucuronidation. Norbuprenorphine has been found to bind opioid receptors in-vitro; however, it has not been studied clinically for opioid-like activity. Naloxone undergoes direct glucuronidation to naloxone-3-glucuronide as well as N-dealkylation, and reduction of the 6-oxo group.

Elimination:

A mass balance study of buprenorphine showed complete recovery of radiolabel in urine (30%) and feces (69%) collected up to 11 days after dosing. Almost all of the dose was accounted for in terms of buprenorphine, norbuprenorphine, and two unidentified buprenorphine metabolites. In urine, most of buprenorphine and norbuprenorphine was conjugated (buprenorphine, 1% free and 9.4% conjugated; norbuprenorphine, 2.7% free and 11% conjugated). In feces, almost all of the buprenorphine and norbuprenorphine were free (buprenorphine, 33% free and 5% conjugated; norbuprenorphine, 21% free and 2% conjugated). Based on all studies performed with Buprenorphine and Naloxone Sublingual Tablets and film, buprenorphine has a mean elimination half-life from plasma ranging from 24 to 42 hours and naloxone has a mean elimination half-life from plasma ranging from 2 to 12 hours.

Drug-Drug Interactions:

CYP3A4 Inhibitors and Inducers: Subjects receiving Buprenorphine and Naloxone Sublingual Tablets should be monitored if inhibitors of CYP3A4 such as azole antifungal agents (e.g., ketoconazole), macrolide antibiotics (e.g., erythromycin) or HIV protease inhibitors and may require dose-reduction of one or both agents. The interaction of buprenorphine with all CYP3A4 inducers has not been studied, therefore it is recommended that patients receiving Buprenorphine and Naloxone Sublingual Tablets be monitored for signs and symptoms of opioid withdrawal if inducers of CYP3A4 (e.g., phenobarbital, carbamazepine, phenytoin, rifampicin) are co-administered [See Drug Interactions (7.1)].

Buprenorphine has been found to be a CYP2D6 and CYP3A4 inhibitor and its major metabolite, norbuprenorphine, has been found to be a moderate CYP2D6 inhibitor in in-vitro studies employing human liver microsomes. However, the relatively low plasma concentrations of buprenorphine and norbuprenorphine resulting from therapeutic doses are not expected to raise significant drug-drug interaction concerns.

Special Populations:

Hepatic Impairment: In a pharmacokinetic study, the disposition of buprenorphine and naloxone were determined after administering a 2 mg/0.5 mg Buprenorphine and Naloxone Sublingual Tablet in subjects with varied degrees of hepatic impairment as indicated by Child-Pugh criteria. The disposition of buprenorphine and naloxone in patients with hepatic impairment were compared to disposition in subjects with normal hepatic function.

In subjects with mild hepatic impairment, the changes in mean Cmax, AUC0-last, and half-life values of both buprenorphine and naloxone were not clinically significant. No dosing adjustment is needed in patients with mild hepatic impairment.

For subjects with moderate and severe hepatic impairment, mean Cmax, AUC0-last, and half-life values of both buprenorphine and naloxone were increased; the effects on naloxone are greater than that on buprenorphine (Table 4).

Table 4. Changes in Pharmacokinetic Parameters in Subjects With Moderate and Severe Hepatic Impairment
Hepatic Impairment | PK Parameters | Increase in buprenorphine compared to healthy subjects | Increase in naloxone compared to healthy subjects
Moderate | Cmax | 8% | 170%
 | AUC0-last | 64% | 218%
 | Half-life | 35% | 165%
Severe | Cmax | 72% | 1030%
 | AUC0-last | 181% | 1302%
 | Half-life | 57% | 122%

The difference in magnitude of the effects on naloxone and buprenorphine are greater in subjects with severe hepatic impairment than subjects with moderate hepatic impairment, and therefore the clinical impact of these effects is likely to be greater in patients with severe hepatic impairment than in patients with moderate hepatic impairment. Buprenorphine/naloxone products should be avoided in patients with severe hepatic impairment and may not be appropriate for patients with moderate hepatic impairment [see Warnings and Precautions (5.12), and Use in Specific Populations (8.6)].

HCV infection: In subjects with HCV infection but no sign of hepatic impairment, the changes in the mean Cmax, AUC0-last, and half-life values of buprenorphine and naloxone were not clinically significant in comparison to healthy subjects without HCV infection. No dosing adjustment is needed in patients with HCV infection.

13 NONCLINICAL TOXICOLOGY

13.1 Carcinogenesis, Mutagenesis, Impairment of Fertility

Carcinogenicity:

A carcinogenicity study of buprenorphine and naloxone (4:1 ratio of the free bases) was performed in Alderley Park rats. Buprenorphine/naloxone was administered in the diet at doses of approximately 7, 31, and 123 mg/kg/day for 104 weeks (estimated exposure was approximately 4, 18, and 44 times the recommended human sublingual dose of 16 mg/4 mg buprenorphine/naloxone based on buprenorphine AUC comparisons). A statistically significant increase in Leydig cell adenomas was observed in all dose groups. No other drug-related tumors were noted.

Carcinogenicity studies of buprenorphine were conducted in Sprague-Dawley rats and CD-1 mice. Buprenorphine was administered in the diet to rats at doses of 0.6, 5.5, and 56 mg/kg/day (estimated exposure was approximately 0.4, 3, and 35 times the recommended human daily sublingual dose of 16 mg on a mg/m^2 basis) for 27 months. As in the buprenorphine/naloxone carcinogenicity study in rat, statistically significant dose-related increases in Leydig cell tumors occurred. In an 86-week study in CD-1 mice, buprenorphine was not carcinogenic at dietary doses up to 100 mg/kg/day (estimated exposure was approximately 30 times the recommended human daily sublingual dose of 16 mg on a mg/m^2 basis).

Mutagenicity:

The 4:1 combination of buprenorphine and naloxone was not mutagenic in a bacterial mutation assay (Ames test) using four strains of S. typhimurium and two strains of E. coli. The combination was not clastogenic in an in vitro cytogenetic assay in human lymphocytes or in an IV micronucleus test in the rat.

Buprenorphine was studied in a series of tests utilizing gene, chromosome, and DNA interactions in both prokaryotic and eukaryotic systems. Results were negative in yeast (S. cerevisiae) for recombinant, gene convertant, or forward mutations; negative in Bacillus subtilis “rec” assay, negative for clastogenicity in CHO cells, Chinese hamster bone marrow and spermatogonia cells, and negative in the mouse lymphoma L5178Y assay.

Results were equivocal in the Ames test: negative in studies in two laboratories, but positive for frame shift mutation at a high dose (5 mg/plate) in a third study. Results were positive in the Green-Tweets (E. coli) survival test, positive in a DNA synthesis inhibition (DSI) test with testicular tissue from mice, for both in vivo and in vitro incorporation of [^3H]thymidine, and positive in unscheduled DNA synthesis (UDS) test using testicular cells from mice.

Impairment of Fertility:

Dietary administration of buprenorphine in the rat at dose levels of 500 ppm or greater (equivalent to approximately 47 mg/kg/day or greater; estimated exposure approximately 28 times the recommended human daily sublingual dose of 16 mg on a mg/m^2 basis) produced a reduction in fertility demonstrated by reduced female conception rates. A dietary dose of 100 ppm (equivalent to approximately 10 mg/kg/day; estimated exposure approximately 6 times the recommended human daily sublingual dose of 16 mg on a mg/m^2 basis) had no adverse effect on fertility.

14 CLINICAL STUDIES

Clinical data on the safety and efficacy of buprenorphine and naloxone were derived from studies of buprenorphine sublingual tablet formulations, with and without naloxone, and from studies of sublingual administration of a more bioavailable ethanolic solution of buprenorphine.

Buprenorphine and Naloxone Sublingual Tablets were studied in 575 patients, buprenorphine sublingual tablets in 1834 patients and buprenorphine sublingual solutions in 2470 patients. A total of 1270 women received buprenorphine in those clinical trials. Dosing recommendations are based on data from one trial of both tablet formulations and two trials of the ethanolic solution. All trials used buprenorphine in conjunction with psychosocial counseling as part of a comprehensive addiction treatment program. There were no clinical studies conducted to assess the efficacy of buprenorphine as the only component of treatment.

In a double-blind placebo- and active-controlled study, 326 heroin-addicted subjects were randomly assigned to either Buprenorphine and Naloxone Sublingual Tablets, 16 mg/4 mg per day; buprenorphine sublingual tablets, 16 mg per day; or placebo sublingual tablets. For subjects randomized to either active treatment, dosing began with one 8 mg buprenorphine on Day 1, followed by 16 mg (two 8 mg tablets) of buprenorphine on Day 2. On Day 3, those randomized to receive Buprenorphine and Naloxone Sublingual Tablets were switched to the combination tablet. Subjects randomized to placebo received one placebo tablet on Day 1 and two placebo tablets per day thereafter for four weeks. Subjects were seen daily in the clinic (Monday through Friday) for dosing and efficacy assessments. Take-home doses were provided for weekends. Subjects were instructed to hold the medication under the tongue for approximately 5 to 10 minutes until completely dissolved. Subjects received counseling regarding HIV infection and up to one hour of individualized counseling per week. The primary study comparison was to assess the efficacy of Buprenorphine and Naloxone Sublingual Tablets and buprenorphine sublingual tablets individually against placebo sublingual tablet. The percentage of thrice-weekly urine samples that were negative for non-study opioids was statistically higher for both Buprenorphine and Naloxone Sublingual Tablets and buprenorphine sublingual tablets than for placebo sublingual tablets.

In a double-blind, double-dummy, parallel-group study comparing buprenorphine ethanolic solution to a full agonist active control, 162 subjects were randomized to receive the ethanolic sublingual solution of buprenorphine at 8 mg/day (a dose which is roughly comparable to a dose of 12 mg/3 mg per day of Buprenorphine and Naloxone Sublingual Tablets or 12 mg per day of buprenorphine sublingual tablets), or two relatively low doses of active control, one of which was low enough to serve as an alternative to placebo, during a 3 to 10 day induction phase, a 16-week maintenance phase and a 7-week detoxification phase. Buprenorphine was titrated to maintenance dose by Day 3; active control doses were titrated more gradually.

Maintenance dosing continued through Week 17, and then medications were tapered by approximately 20% to 30% per week over Weeks 18 to 24, with placebo dosing for the last two weeks. Subjects received individual and/or group counseling weekly.

Based on retention in treatment and the percentage of thrice-weekly urine samples negative for non-study opioids, buprenorphine was more effective than the low dose of the control, in keeping heroin addicts in treatment and in reducing their use of opioids while in treatment. The effectiveness of buprenorphine, 8 mg per day was similar to that of the moderate active control dose, but equivalence was not demonstrated.

In a dose-controlled, double-blind, parallel-group, 16-week study, 731 subjects were randomized to receive one of four doses of buprenorphine ethanolic solution: 1 mg, 4 mg, 8 mg, and 16 mg. Buprenorphine was titrated to maintenance doses over 1 to 4 days and continued for 16 weeks. Subjects received at least one session of AIDS education and additional counseling ranging from one hour per month to one hour per week, depending on site.

Based on retention in treatment and the percentage of thrice-weekly urine samples negative for non-study opioids, the three highest tested doses were superior to the 1 mg dose. Therefore, this study showed that a range of buprenorphine doses may be effective. The 1 mg dose of buprenorphine sublingual solution can be considered to be somewhat lower than a 2 mg tablet dose. The other doses used in the study encompass a range of tablet doses from approximately 6 mg to approximately 24 mg.

16 HOW SUPPLIED / STORAGE AND HANDLING

Buprenorphine and Naloxone Sublingual Tablets are uncoated, white to off-white, round, biconvex tablet, debossed with a “↑” logo on one side and an "N8" indicating the 8 mg/2 mg strength on the other side, supplied in white HDPE bottles:

BOTTLES of 30 tablets

- NDC 53217-138-30, buprenorphine and naloxone 8 mg /2 mg.

Store at 25°C (77°F), excursions permitted to 15-30°C (59-86°F) [see USP Controlled Room Temperature].

Patients should be advised to store buprenorphine-containing medications safely and out of sight and reach of children. Destroy any unused medication appropriately [see Disposal of Unused Buprenorphine and Naloxone Sublingual Tablets (17)].

Repackaged by

Aidarex Pharmaceuticals, LLC

Corona, CA 92880

17 PATIENT COUNSELING INFORMATION

See FDA-approved patient labeling (Medication Guide)

Safe Use

Before initiating treatment with Buprenorphine and Naloxone Sublingual Tablets, explain the points listed below to caregivers and patients. Instruct patients to read the Medication Guide each time buprenorphine and naloxone is dispensed because new information may be available.

- Patients should be warned that it is extremely dangerous to self-administer non-prescribed benzodiazepines or other CNS depressants (including alcohol) while taking Buprenorphine and Naloxone Sublingual Tablets. Patients prescribed benzodiazepines or other CNS depressants should be cautioned to use them only as directed by their physician [see Warnings and Precautions (5.2), Drug Interactions (7.3)].
- Patients should be advised that Buprenorphine and Naloxone Sublingual Tablets contain an opioid that can be a target for people who abuse prescription medications or street drugs. Patients should be cautioned to keep their tablets in a safe place, and to protect them from theft.
- Patients should be instructed to keep Buprenorphine and Naloxone Sublingual Tablets in a secure place, out of the sight and reach of children. Accidental or deliberate ingestion by a child may cause respiratory depression that can result in death. Patients should be advised that if a child is exposed to Buprenorphine and Naloxone Sublingual Tablets, medical attention should be sought immediately.
- Inform patients that Buprenorphine and Naloxone Sublingual Tablets could cause a rare but potentially life-threatening condition resulting from concomitant administration of serotonergic drugs. Warn patients of the symptoms of serotonin syndrome and to seek medical attention right away if symptoms develop. Instruct patients to inform their physicians if they are taking, or plan to take serotonergic medications [see Drug Interactions (7.4)].
- Inform patients that Buprenorphine and Naloxone Sublingual Tablets could cause adrenal insufficiency, a potentially life-threatening condition. Adrenal insufficiency may present with non-specific symptoms and signs such as nausea, vomiting, anorexia, fatigue, weakness, dizziness, and low blood pressure. Advise patients to seek medical attention if they experience a constellation of these symptoms [see Warnings and Precautions (5.6)].
- Patients should be advised never to give Buprenorphine and Naloxone Sublingual Tablets to anyone else, even if he or she has the same signs and symptoms. It may cause harm or death.
- Patients should be advised that selling or giving away this medication is against the law.
- Patients should be cautioned that Buprenorphine and Naloxone Sublingual Tablets may impair the mental or physical abilities required for the performance of potentially dangerous tasks such as driving or operating machinery. Caution should be taken especially during drug induction and dose adjustment and until individuals are reasonably certain that buprenorphine therapy does not adversely affect their ability to engage in such activities [see Warnings and Precautions (5.12)].
- Patients should be advised not to change the dosage of Buprenorphine and Naloxone Sublingual Tablets without consulting their physician.
- Patients should be advised to take Buprenorphine and Naloxone Sublingual Tablets once a day.
- Patients should be informed that Buprenorphine and Naloxone Sublingual Tablets can cause drug dependence and that withdrawal signs and symptoms may occur when the medication is discontinued.
- Patients seeking to discontinue treatment with buprenorphine for opioid dependence should be advised to work closely with their physician on a tapering schedule and should be apprised of the potential to relapse to illicit drug use associated with discontinuation of opioid agonist/partial agonist medication-assisted treatment.
- Patients should be cautioned that, like other opioids Buprenorphine and Naloxone Sublingual Tablets may produce orthostatic hypotension in ambulatory individuals [see Warnings and Precautions. (5.13].
- Patients should inform their physician if any other prescription medications, over-the-counter medications, or herbal preparations are prescribed or currently being used [see Drug Interactions (7.1, 7.2 and 7.3)]
- Advise women that if they are pregnant while being treated with Buprenorphine and Naloxone Sublingual Tablets, the baby may have signs of withdrawal at birth and that withdrawal is treatable [see Warnings and Precautions [see Warnings and Precautions (5.5), Use in Specific Populations (8.1)].
- Patients should be warned that buprenorphine passes into breast milk. Breast-feeding is not advised in mothers treated with buprenorphine products [see Use in Specific Populations (8.3)].
- Patients should inform their family members that, in the event of emergency, the treating physician or emergency room staff should be informed that the patient is physically dependent on an opioid and that the patient is being treated with Buprenorphine and Naloxone Sublingual Tablets.
- Refer to the Medication Guide for additional information regarding the counseling information.

Disposal of Unused Buprenorphine and Naloxone Sublingual Tablets

Unused Buprenorphine and Naloxone Sublingual Tablets should be disposed of as soon as they are no longer needed. Unused tablets should be flushed down the toilet.

Manufactured by:
Ethypharm S.A.
76121 Le Grand Quevilly Cedex
France

Made in France

Distributed by:
Hi-Tech Pharmacal Co., Inc.
Amityville, NY 11701
Tel: 1-888-775-1770
www.hitechpharm.com/drugsafety

Rev. 287/294:02 11/2016

MEDICATION GUIDE

BUPRENORPHINE (byoo-pre-NOR-feen) AND NALOXONE (nah-LOX-own)

SUBLINGUAL TABLETS (CIII)

Rx Only

IMPORTANT:
Keep Buprenorphine and Naloxone Sublingual Tablets in a secure place away from children. Accidental use by a child is a medical emergency and can result in death. If a child accidentally uses Buprenorphine and Naloxone Sublingual Tablets, get emergency help right away.

Read this Medication Guide before you start taking Buprenorphine and Naloxone Sublingual Tablets and each time you get a refill. There may be new information. This Medication Guide does not take the place of talking to your doctor. Talk to your doctor or pharmacist if you have questions about Buprenorphine and Naloxone Sublingual Tablets.

Share the important information in this Medication Guide with members of your household.

What is the most important information I should know about Buprenorphine and Naloxone Sublingual Tablets?

- Buprenorphine and Naloxone Sublingual Tablets can cause serious and life-threatening breathing problems. Call your doctor right away or get emergency help if:
  - You feel faint, dizzy, or confused
  - Your breathing gets much slower than is normal for you

These can be signs of an overdose or other serious problems.

- Buprenorphine and Naloxone Sublingual Tablets contains an opioid that can cause physical dependence.
  - Do not stop taking Buprenorphine and Naloxone Sublingual Tablets without talking to your doctor. You could become sick with uncomfortable withdrawal signs and symptoms because your body has become used to this medicine
  - Physical dependence is not the same as drug addiction
  - Buprenorphine and Naloxone Sublingual Tablets is not for occasional or “as needed” use
- An overdose, and even death, can happen if you take benzodiazepines, sedatives, tranquilizers, or alcohol while using Buprenorphine and Naloxone Sublingual Tablets. Ask your doctor what you should do if you are taking one of these.
- Call a doctor or get emergency help right away if you:
  - Feel sleepy and uncoordinated
  - Have blurred vision
  - Have slurred speech
  - Cannot think well or clearly
  - Have slowed reflexes and breathing
- Do not inject (“shoot-up”) Buprenorphine and Naloxone Sublingual Tablets.
  - Injecting this medicine may cause life-threatening infections and other serious health problems.
  - Injecting Buprenorphine and Naloxone Sublingual Tablets may cause serious withdrawal symptoms such as pain, cramps, vomiting, diarrhea, anxiety, sleep problems, and cravings.
- In an emergency, have family members tell the emergency department staff that you are physically dependent on an opioid and are being treated with Buprenorphine and Naloxone Sublingual Tablets.

What are Buprenorphine and Naloxone Sublingual Tablets?

- Buprenorphine and Naloxone Sublingual Tablet is a prescription medicine used to treat adults who are addicted to (dependent on) opioid drugs (either prescription or illegal); as part of a complete treatment program that also includes counseling and behavioral therapy.

Buprenorphine and Naloxone Sublingual Tablets are a controlled substance (CIII) because they contain buprenorphine, which can be a target for people who abuse prescription medicines or street drugs. Keep your Buprenorphine and Naloxone Sublingual Tablets in a safe place to protect them from theft. Never give your Buprenorphine and Naloxone Sublingual Tablets to anyone else; it can cause death or harm them. Selling or giving away this medicine is against the law.

- It is not known if Buprenorphine and Naloxone Sublingual Tablets are safe or effective in children.

Who should not take Buprenorphine and Naloxone Sublingual Tablets?

Do not take Buprenorphine and Naloxone Sublingual Tablets if you are allergic to buprenorphine or naloxone.

What should I tell my doctor before taking Buprenorphine and Naloxone Sublingual Tablets?

Buprenorphine and Naloxone Sublingual Tablets may not be right for you. Before taking Buprenorphine and Naloxone Sublingual Tablets, tell your doctor if you:

- Have trouble breathing or lung problems
- Have an enlarged prostate gland (men)
- Have a head injury or brain problem
- Have problems urinating
- Have a curve in your spine that affects your breathing
- Have liver or kidney problems
- Have gallbladder problems
- Have adrenal gland problems
- Have Addison’s disease
- Have low thyroid (hypothyroidism)
- Have a history of alcoholism
- Have mental problems such as hallucinations (seeing or hearing things that are not there)
- Have any other medical condition
- Are pregnant or plan to become pregnant. If you take Buprenorphine and Naloxone Sublingual Tablets while pregnant, your baby may have symptoms of opioid withdrawal or respiratory depression at birth. Talk to your doctor if you are pregnant or plan to become pregnant.
- Are breast feeding or plan to breast feed. Buprenorphine HCL and naloxone HCL can pass into your milk and may harm the baby. Talk to your doctor about the best way to feed your baby if you take Buprenorphine and Naloxone Sublingual Tablets. Breast feeding is not recommended while taking Buprenorphine and Naloxone Sublingual Tablets.

Tell your doctor about all the medicines you take, including prescription and nonprescription medicines, vitamins and herbal supplements. Buprenorphine and Naloxone Sublingual Tablets may affect the way other medicines work and other medicines may affect how Buprenorphine and Naloxone Sublingual Tablets work. Some medicines may cause serious or life-threatening medical problems when taken with Buprenorphine and Naloxone Sublingual Tablets.

Sometimes the doses of certain medicines and Buprenorphine and Naloxone Sublingual Tablets may need to be changed if used together. Do not take any medicine while using Buprenorphine and Naloxone Sublingual Tablets until you have talked with your doctor. Your doctor will tell you if it is safe to take other medicines while you are using Buprenorphine and Naloxone Sublingual Tablets.

Be especially careful about taking other medicines that may make you sleepy, such as pain medicines, tranquilizers, antidepressant medicines, sleeping pills, anxiety medicines or antihistamines.

Know the medicines you take. Keep a list of them to show your doctor or pharmacist each time you get a new medicine.

How should I take Buprenorphine and Naloxone Sublingual Tablets?

- Always take Buprenorphine and Naloxone Sublingual Tablets exactly as your doctor tells you. Your doctor may change your dose after seeing how it affects you. Do not change your dose unless your doctor tells you to change it.
- Do not take Buprenorphine and Naloxone Sublingual Tablets more often than prescribed by your doctor.
- If you are prescribed a dose of 2 or more Buprenorphine and Naloxone Sublingual Tablets at the same time:
  - Ask your doctor for instructions on the right way to take Buprenorphine and Naloxone Sublingual Tablets
  - Follow the same instructions every time you take a dose of Buprenorphine and Naloxone Sublingual Tablets
- Put the tablets under your tongue. Let them dissolve completely

- While Buprenorphine and Naloxone Sublingual Tablets are dissolving, do not chew or swallow the tablet because the medicine will not work as well.
- Talking while the tablet is dissolving can affect how well the medicine in Buprenorphine and Naloxone Sublingual Tablets are absorbed.
- If you miss a dose of Buprenorphine and Naloxone Sublingual Tablets, take your medicine when you remember. If it is almost time for your next dose, skip the missed dose and take the next dose at your regular time. Do not take 2 doses at the same time unless your doctor tells you to. If you are not sure about your dosing, call your doctor.
- Do not stop taking Buprenorphine and Naloxone Sublingual Tablets suddenly. You could become sick and have withdrawal symptoms because your body has become used to the medicine. Physical dependence is not the same as drug addiction. Your doctor can tell you more about the differences between physical dependence and drug addiction. To have fewer withdrawal symptoms, ask your doctor how to stop using Buprenorphine and Naloxone Sublingual Tablets the right way.
- If you take too much Buprenorphine and Naloxone Sublingual Tablets or overdose, call Poison Control or get emergency medical help right away.

What should I avoid while taking Buprenorphine and Naloxone Sublingual Tablets?

- Do not drive, operate heavy machinery, or perform any other dangerous activities until you know how this medication affects you. Buprenorphine can cause drowsiness and slow reaction times. This may happen more often in the first few weeks of treatment when your dose is being changed, but can also happen if you drink alcohol or take other sedative drugs when you take Buprenorphine and Naloxone Sublingual Tablets.
- You should not drink alcohol while using Buprenorphine and Naloxone Sublingual Tablets, as this can lead to loss of consciousness or even death.

What are the possible side effects of Buprenorphine and Naloxone Sublingual Tablets?

Buprenorphine and Naloxone Sublingual Tablets can cause serious side effects including:

- See “What is the most important information I should know about Buprenorphine and Naloxone Sublingual Tablets?”
- Respiratory problems. You have a higher risk of death and coma if you take Buprenorphine and Naloxone Sublingual Tablets with other medicines, such as benzodiazepines.
- Sleepiness, dizziness, and problems with coordination
- Dependency or abuse
- Liver problems. Call your doctor right away if you notice any of these signs of liver problems: Your skin or the white part of your eyes turning yellow (jaundice), urine turning dark, stools turning light in color, you have less of an appetite, or you have stomach (abdominal) pain or nausea. Your doctor should do tests before you start taking and while you take Buprenorphine and Naloxone Sublingual Tablets.
- Allergic reaction. You may have a rash, hives, swelling of your face, wheezing, or loss of blood pressure and consciousness. Call a doctor or get emergency help right away.
- Opioid withdrawal. This can include: shaking, sweating more than normal, feeling hot or cold more than normal, runny nose, watery eyes, goose bumps, diarrhea, vomiting and muscle aches. Tell your doctor if you develop any of these symptoms.
- Decrease in blood pressure. You may feel dizzy if you get up too fast from sitting or lying down.

Common side effects of Buprenorphine and Naloxone Sublingual Tablets include:

- Headache
- Nausea
- Vomiting
- Increased sweating
- Constipation
- Drug withdrawal syndrome
- Decrease in sleep (insomnia)
- Pain
- Swelling of the extremities

Tell your doctor about any side effect that bothers you or that does not go away.

These are not all the possible side effects of Buprenorphine and Naloxone Sublingual Tablets. For more information, ask your doctor or pharmacist.

Call your doctor for medical advice about side effects. You may report side effects to FDA at 1-800-FDA-1088.

How should I store Buprenorphine and Naloxone Sublingual Tablets?

- Store Buprenorphine and Naloxone Sublingual Tablets at room temperature
- Keep Buprenorphine and Naloxone Sublingual Tablets in a safe place, out of the sight and reach of children.

How should I dispose of unused Buprenorphine and Naloxone Sublingual Tablets?

- Dispose of unused Buprenorphine and Naloxone Sublingual Tablets as soon as you no longer need them.
- Flush unused tablets down the toilet.

General information about the safe and effective use of Buprenorphine and Naloxone Sublingual Tablets.

Medicines are sometimes prescribed for purposes other than those listed in a Medication Guide. Do not use Buprenorphine and Naloxone Sublingual Tablets for a condition for which it was not prescribed. Do not give Buprenorphine and Naloxone Sublingual Tablets to other people, even if they have the same symptoms you have. It may harm them and it is against the law.

This Medication Guide summarizes the most important information about Buprenorphine and Naloxone Sublingual Tablets. If you would like more information, talk to your doctor or pharmacist. You can ask your doctor or pharmacist for information that is written for healthcare professionals.

For more information call 1-888-775-1770.

What are the ingredients in Buprenorphine and Naloxone Sublingual Tablets?

Active Ingredients: buprenorphine hydrochloride and naloxone hydrochloride
Inactive Ingredients: lactose monohydrate, mannitol, cornstarch, povidone, purified water, citric acid anhydrous, sodium citrate, sodium stearyl fumarate, acesulfame K sweetener, a lemon flavor and a lime flavor

Manufactured by:
Ethypharm S.A.
76121 Le Grand Quevilly Cedex
France

Distributed by:
Hi-Tech Pharmacal Co., Inc.
Amityville, NY 11701
Tel: 1-888-775-1770
www.hitechpharm.com/drugsafety

This Medication Guide has been approved by the U.S. Food and Drug Administration.

Revised - November 2016

PRINCIPAL DISPLAY PANEL

SPL Label